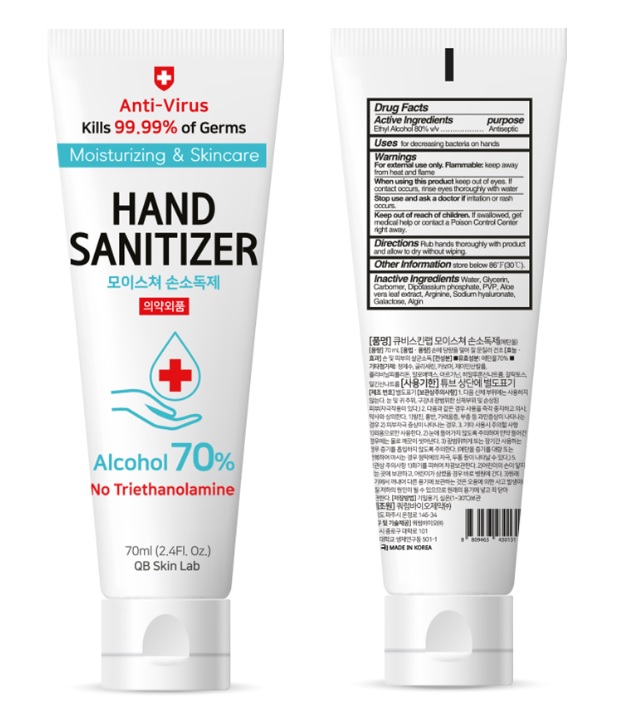 DRUG LABEL: QB Skin Lab Hand Sanitizer
NDC: 75710-078 | Form: GEL
Manufacturer: Quorum Bio Pharmaceutical Co., Ltd.
Category: otc | Type: HUMAN OTC DRUG LABEL
Date: 20200421

ACTIVE INGREDIENTS: ALCOHOL 56 mL/70 mL
INACTIVE INGREDIENTS: GALACTOSE; SODIUM ALGINATE; POVIDONE, UNSPECIFIED; HYALURONATE SODIUM; GLYCERIN; DIBASIC POTASSIUM PHOSPHATE; CARBOMER HOMOPOLYMER, UNSPECIFIED TYPE; WATER; ALOE VERA LEAF; ARGININE

QB Skin Lab Hand Sanitizer 70 ml : 75710-078-01